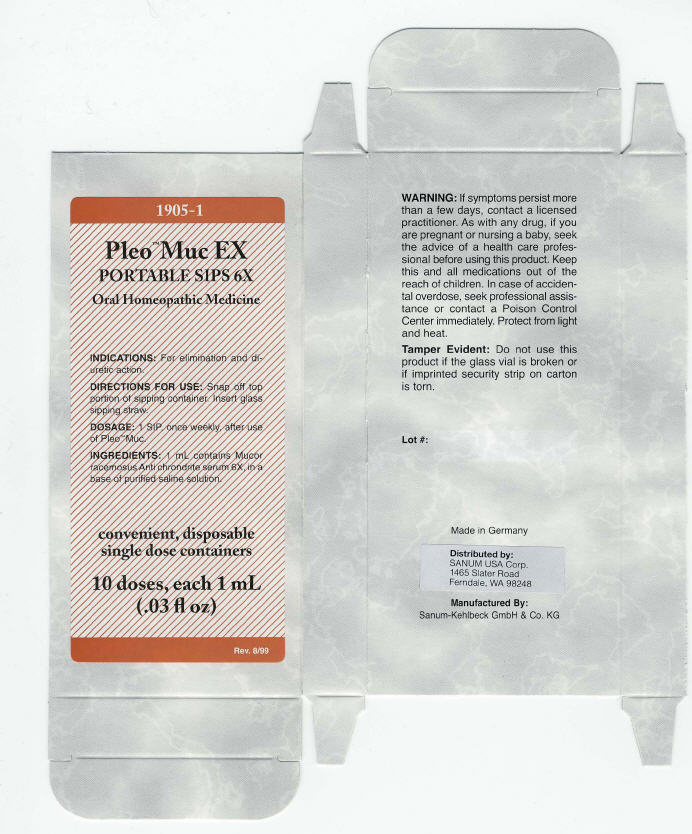 DRUG LABEL: Pleo Muc Ex
NDC: 60681-1905 | Form: LIQUID
Manufacturer: Sanum Kehlbeck GmbH & Co. KG
Category: homeopathic | Type: HUMAN OTC DRUG LABEL
Date: 20100203

ACTIVE INGREDIENTS: Mucor racemosus immunoserum rabbit 6 [hp_X]/1 mL
INACTIVE INGREDIENTS: sodium chloride; water

Pleo™ Muc EX
PORTABLE SIPS 6X

Oral Homeopathic Medicine

10 doses, each 1 mL
(.03 fl oz)

INDICATIONS

For elimination and diuretic action.

DIRECTIONS FOR USE

Snap off top portion of sipping container. Insert glass sipping straw.

DOSAGE

1 SIP, once weekly, after use of Pleo™ Muc.

INGREDIENTS

1 mL contains Mucor racemosus Anti chrondrite serum 6X, in a base of purified saline solution.

WARNING

If symptoms persist more than a few days, contact a licensed practitioner. As with any drug, if you are pregnant or nursing a baby, seek the advice of a health care professional before using this product.

KEEP OUT OF REACH OF CHILDREN

Keep this and all medications out of the reach of children. In case of accidental overdose, seek professional assistance or contact a Poison Control Center immediately.

STORAGE AND HANDLING

Protect from light and heat.

Tamper Evident

Do not use this product if the glass vial is broken or if imprinted security strip on carton is torn.

Made in Germany

Distributed by:
SANUM USA Corp.
1465 Slater Road
Ferndale, WA 98248

Manufactured By:
Sanum-Kehlbeck GmbH & Co. KG

Rev. 8/99

PRINCIPAL DISPLAY PANEL - 1 mL Vial Carton

1905-1

Pleo™ Muc EX
PORTABLE SIPS 6X

Oral Homeopathic Medicine

INDICATIONS: For elimination and di-
uretic action.

DIRECTIONS FOR USE: Snap off top
portion of sipping container. Insert glass
sipping straw.

DOSAGE: 1 SIP, once weekly, after use
of Pleo™ Muc.

INGREDIENTS: 1 mL contains Mucor
racemosus Anti chrondrite serum 6X, in a
base of purified saline solution.

convenient, disposable
single dose containers

10 doses, each 1 mL
(.03 fl oz)

Rev. 8/99